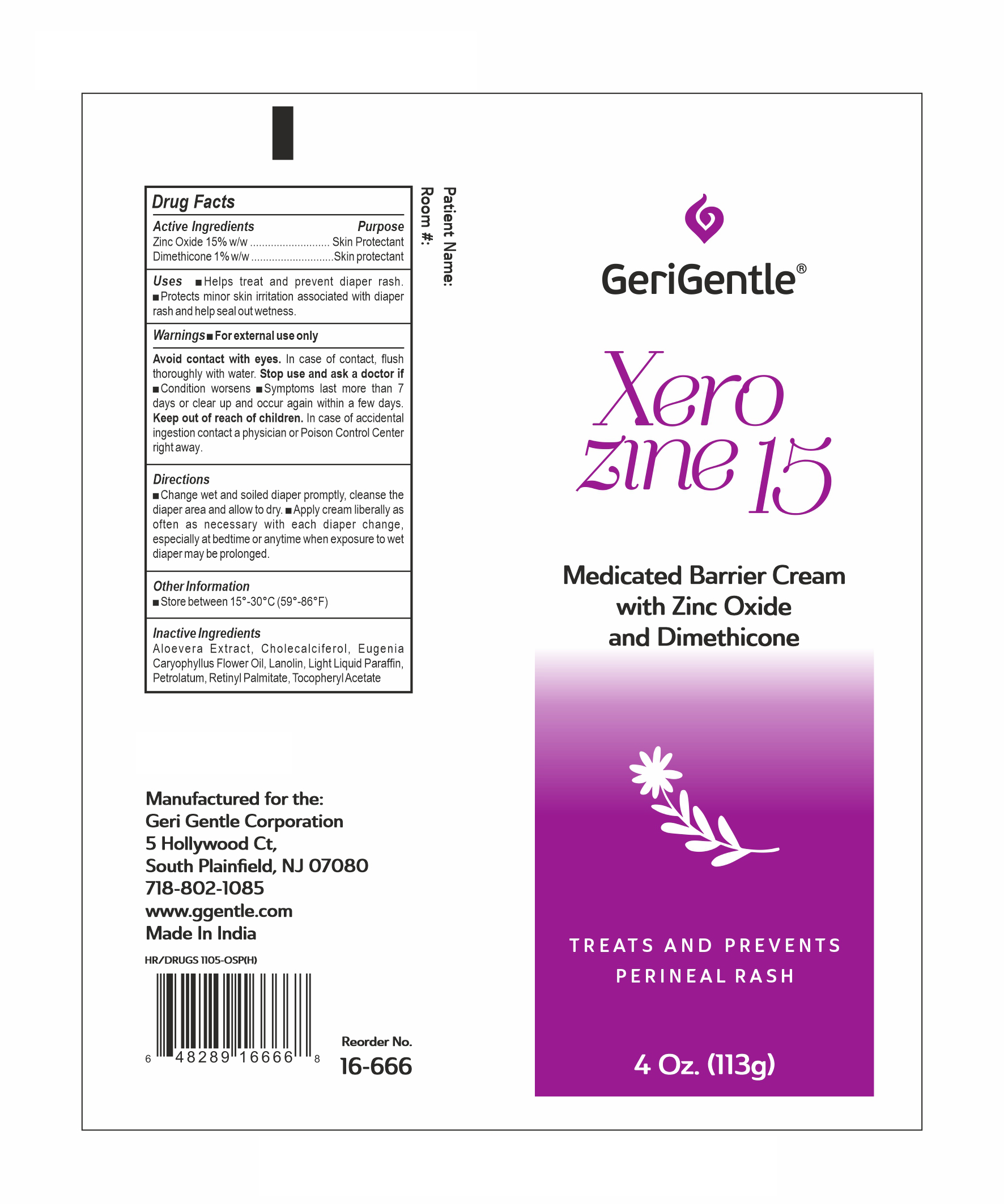 DRUG LABEL: GG XEROZINE 15
NDC: 69771-022 | Form: OINTMENT
Manufacturer: GERI-GENTLE CORPORATION
Category: otc | Type: HUMAN OTC DRUG LABEL
Date: 20260114

ACTIVE INGREDIENTS: ZINC OXIDE 15 g/100 g; DIMETHICONE 1 g/100 g
INACTIVE INGREDIENTS: ALPHA-TOCOPHEROL ACETATE; PETROLATUM; LIGHT MINERAL OIL; CHOLECALCIFEROL; ALOE VERA LEAF; CLOVE LEAF OIL; LANOLIN; VITAMIN A PALMITATE

GG XEROZINE 15

Active Ingredients:

Zinc Oxide 15%

Dimethicone 1%

Purpose:

Skin Protectant

Uses:

- Helps treat and prevent diaper rash.
- Protects minor skin irritation associated with

diaper rash and helps seal out wetness.

Warnings:

- For external use only,
- Avoid contact with eyes, In case of contact, flush thoroughly with water.

Warnings:

Stop use and ask a doctor If

• condition worsens
• symptoms last more than 7 days or clear up and
occur again within a few days.

Warnings:

Keep out of reach of children.

In case of accidental ingestion contact a physician or Poison Control Center right away.

Directions:

- Change wet and soiled diapers promptly, cleanse the diaper area and allow to dry.
- Apply cream liberally as often as necessary, with each diaper change, especially at bedtime or anytime when exposure to wet diapers may be prolonged.

Other Information:

- Store between 15-30 °C

Inactive Ingredients:

Aloe vera Extract, Cholecalciferol, Eugenia Caryophyllus Flower Oil, Lanolin, Light Liquid Parafﬁn, Petrolatum, Retinyl Palmitate,Tocopheryl Acetate